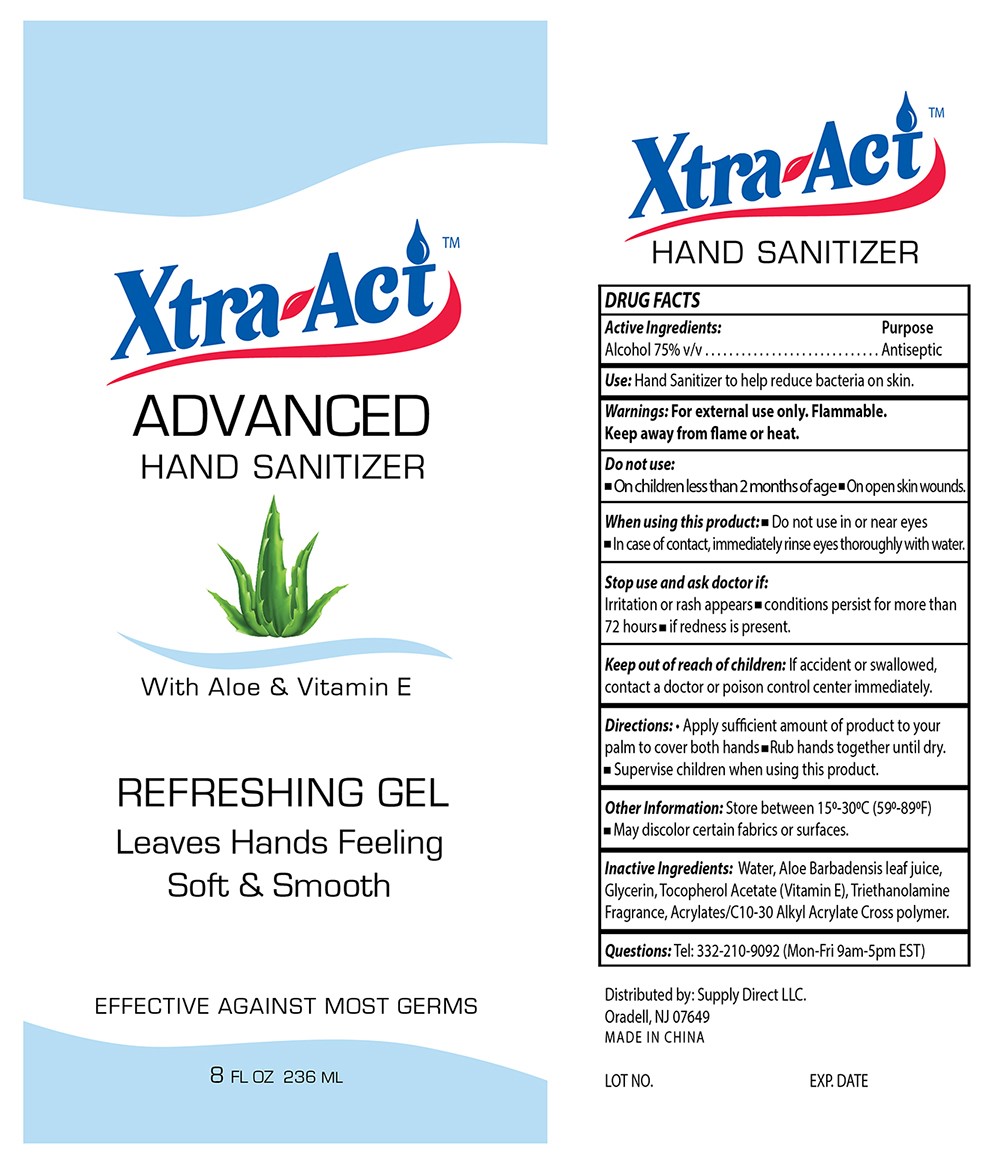 DRUG LABEL: Hand Sanitizer
NDC: 76383-058 | Form: GEL
Manufacturer: BBC GROUP LIMITED
Category: otc | Type: HUMAN OTC DRUG LABEL
Date: 20200609

ACTIVE INGREDIENTS: ALCOHOL 75 mL/100 mL
INACTIVE INGREDIENTS: ALOE VERA LEAF; GLYCERIN; WATER; CARBOMER INTERPOLYMER TYPE A (55000 CPS); TROLAMINE; .ALPHA.-TOCOPHEROL ACETATE

Alcohol 75 Hand Sanitizer

Active Ingredient

Alcohol 75% v/v

Purpose

Antiseptic

Use

Hand sanitizer to help reduce bacteria on skin

Warnings

For external use only. Flammable. Keep away from flame or heat.

Do not use

■ On children less than 2 months of age ■ On open skin wounds

When using this product

■ Do not use in or near eyes. ■ In case of contact, immediately rinse eyes throughly with water.

Stop use and ask a doctor if

Irritation or rash appears ■ conditions persist for more than 72 hours ■ if redness is present

Keep out of reach of children

If accident or swallowed, contact a doctor or poison control center immediately.

Directions

■ Apply a dime sized amount to hands. Rub hands together until dry ■ Supervise children under 6 years of age when using this product to avoid swallowing

Other information

Store between 15º-30ºC (59-86ºF). ■ May discolor certain fabrics or surfaces

Inactive ingredients

Water, Aloe Barbadensis leaf juice, Glycerin, Tocopheryl Acetate (Vitamin E), Triethanolamine, Fragrance, Acrylates/C10-30 Alkyl Acrylate Crosspolymer

Questions

Tel: 332-210-9092 (Mon-Fri 9am-5pm EST)